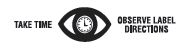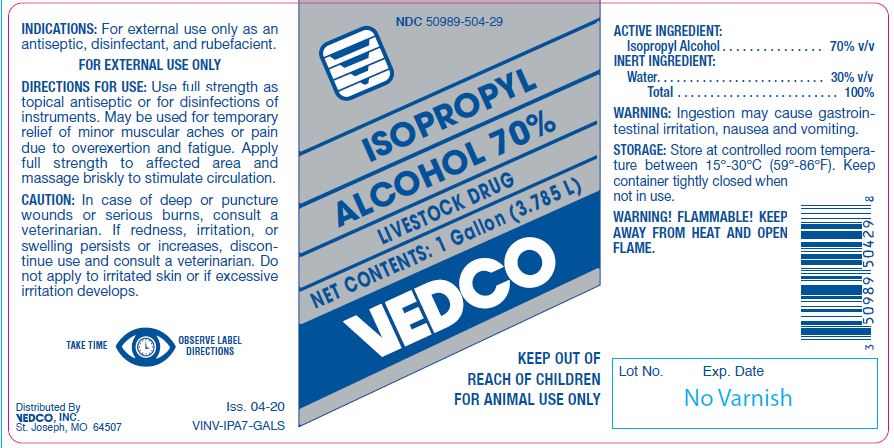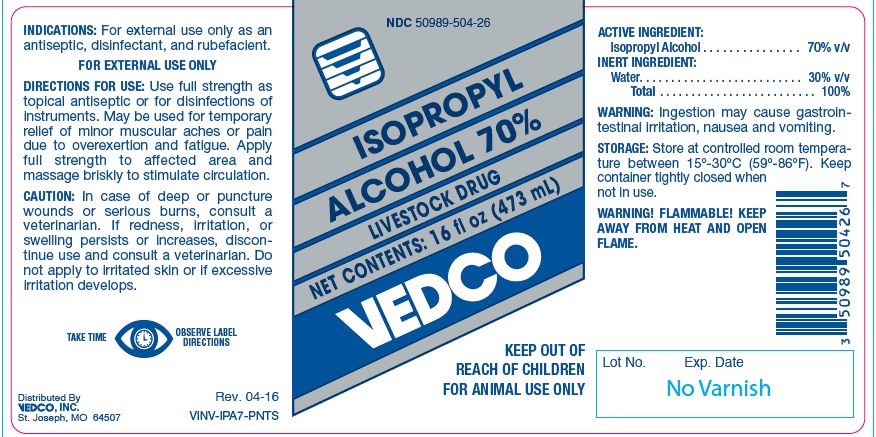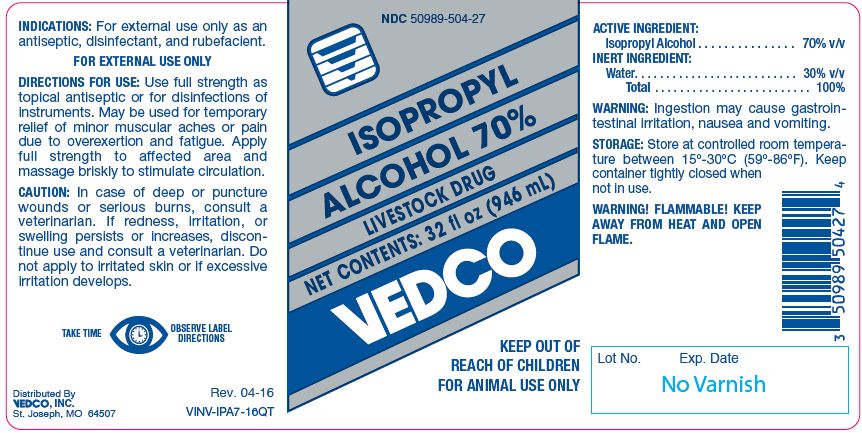 DRUG LABEL: Isopropyl Alcohol
NDC: 50989-504 | Form: SOLUTION
Manufacturer: Vedco, Inc.
Category: animal | Type: OTC ANIMAL DRUG LABEL
Date: 20241029

ACTIVE INGREDIENTS: ISOPROPYL ALCOHOL 557.25 g/1 L

ISOPROPYL ALCOHOL 70%
LIVESTOCK DRUG

KEEP OUT OF REACH OF CHILDREN
FOR ANIMAL USE ONLY

INDICATIONS:

For external use only as an antiseptic, disinfectant, and rubefacient.
FOR EXTERNAL USE ONLY

DIRECTIONS FOR USE:

Use full strength as topical antiseptic or for disinfections of instruments. May be used for temporary relief of minor muscular aches or pain due to overexertion and fatigue. Apply full strength to affected area and massage briskly to stimulate circulation.

CAUTION:

In case of deep or puncture wounds or serious burns, consult a veterinarian. If redness, irritation, or swelling persists or increases, discontinue use and consult a veterinarian. Do not apply to irritated skin or if excessive irritation develops.

ACTIVE INGREDIENT:

Isopropyl Alcohol . . . . . . . . . . . . . . . 70% v/v

INERT INGREDIENT:

Water. . . . . . . . . . . . . . . . . . . . . . . . . . 30% v/v
Total . . . . . . . . . . . . . . . . . . . . . . . . . 100%

WARNING:

Ingestion may cause gastrointestinal irritation, nausea and vomiting

STORAGE:

Store at controlled room temperature between 15º-30ºC (59º-86ºF). Keep container tightly closed when not in use.

WARNINGS AND PRECAUTIONS

WARNING! FLAMMABLE! KEEP AWAY FROM HEAT AND OPEN FLAME.

Net Contents:

16 fl oz (473 mL) VINV-IPA7-PNTS

32 fl oz (960 mL) VINV-IPA7-16QT

1 Gallon (3.785 L) VINV-IPA7-GALS

INFORMATION FOR OWNERS/CAREGIVERS

Distributed By
VEDCO, INC.
St. Joseph, MO 64507